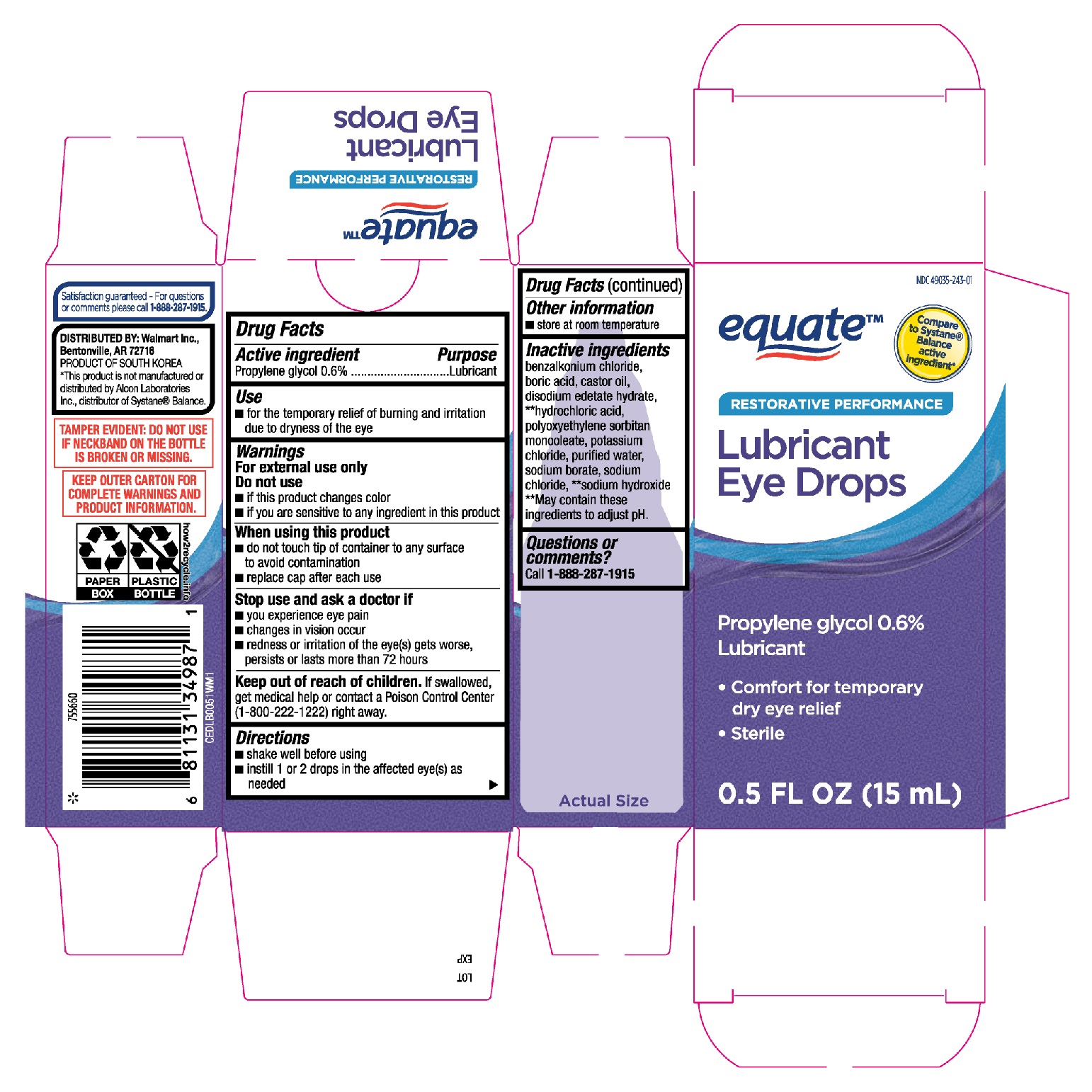 DRUG LABEL: Equate Lubricant Eye Drops Restorative Performance
NDC: 49035-243 | Form: SOLUTION/ DROPS
Manufacturer: Wal-Mart Stores, Inc.
Category: otc | Type: HUMAN OTC DRUG LABEL
Date: 20251230

ACTIVE INGREDIENTS: PROPYLENE GLYCOL 0.6 g/100 mL
INACTIVE INGREDIENTS: BENZALKONIUM CHLORIDE; BORIC ACID; CASTOR OIL; EDETATE DISODIUM; HYDROCHLORIC ACID; PEG-6 SORBITAN OLEATE; POTASSIUM CHLORIDE; WATER; SODIUM BORATE; SODIUM HYDROXIDE; SODIUM CHLORIDE

Equate Restorative Performance Lubricant Eye Drops 15mL (PLD)

Active ingredient

Propylene glycol 0.6%

Purpose

Lubricant

Use

- for the temporary relief of burning and irritation due to dryness of the eye

Warnings

For external use only.

Do not use

- if this product changes color
- if you are sensative to any ingredient in this product

When using this product

- do not touch tip of container to any surface to avoid contamination
- replace cap after each use

Stop use and ask a doctor if

- you experience eye pain
- changes in vision occur
- redness or irritation of the eye(s) gets worse, persists or lasts more than 72 hours

Keep out of reach of children.

If swallowed, get medical help or contact a Poison Control Center (1-800-222-1222) right away.

Directions

- shake well before using
- instill 1 or 2 drops in the affected eye(s) as needed

Other information

- store at room temperature

Inactive ingredients

benzalkonium chloride, boric acid, castor oil, disodium edetate hydrate, **hydrochloric acid, polyoxyethylene sorbitan monooleate, potassium chloride, purified water, sodium borate, sodium chloride, **sodium hydroxide.

**May contain these ingredients to adjust pH.

Questions or comments?

1-888-287-1915